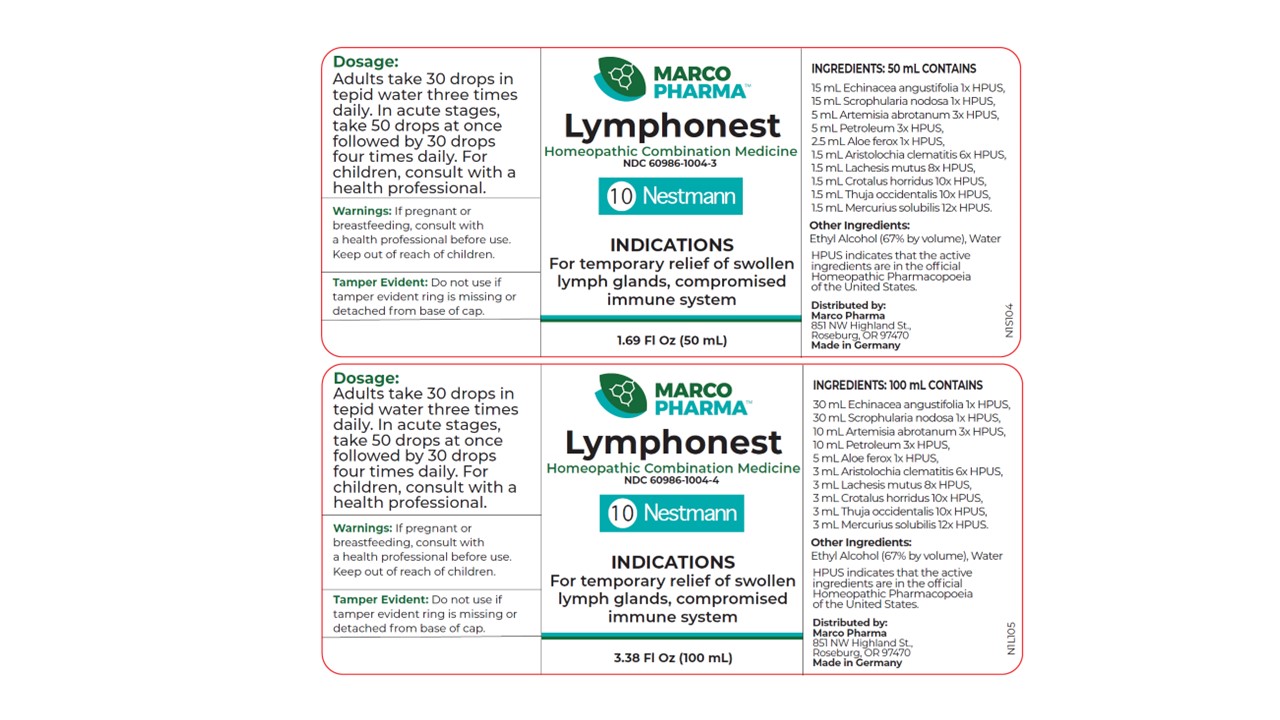 DRUG LABEL: Lymphonest
NDC: 60986-1004 | Form: LIQUID
Manufacturer: Marco Pharma International LLC.
Category: homeopathic | Type: HUMAN OTC DRUG LABEL
Date: 20260112

ACTIVE INGREDIENTS: ECHINACEA ANGUSTIFOLIA 1 [hp_X]/100 mL; SCROPHULARIA NODOSA 1 [hp_X]/100 mL; ARTEMISIA ABROTANUM FLOWERING TOP 3 [hp_X]/100 mL; KEROSENE 3 [hp_X]/100 mL; ALOE 1 [hp_X]/100 mL; MERCURIUS SOLUBILIS 12 [hp_X]/100 mL; CROTALUS HORRIDUS HORRIDUS VENOM 10 [hp_X]/100 mL; THUJA OCCIDENTALIS LEAFY TWIG 10 [hp_X]/100 mL; LACHESIS MUTA VENOM 8 [hp_X]/100 mL; ARISTOLOCHIA CLEMATITIS ROOT 6 [hp_X]/100 mL
INACTIVE INGREDIENTS: ALCOHOL; WATER

Drug Facts

Active Ingredients

Coneflower 1x HPUS

Figwort 1x HPUS

Southernwood 3x HPUS

Kerosine 3x HPUS

Cape Aloe 1x HPUS

Hahnemann's soluble mercury 12x HPUS

Timber rattlesnake 10x HPUS

White cedar 10x HPUS

Bushmaster Viper 8x HPUS

Birthwort 6x HPUS

The letters HPUS indicates that the components in this product are officially monographed in the Homeopathic Pharmacopoeia of United Sates.

Purpose

For relief of swollen lymph glands; suppressed immune functions.

Keep out of reach of children.

Suggested use

30 drops in water 3 times daily. In acute stages, take 50 drops at once followed by 30 drops 4 times daily. Children receive one half or less of the adult amount.

Warnings

If pregnant or breast-feeding, consult a health professional before use. In case of accidental overdose, seek professional assistance or contact a poison control center immediately.

DOSAGE AND ADMINISTRATION

(Read Suggested Use Section)

Inactive Ingredients

Ethyl Alcohol (63% by vol.) and Water